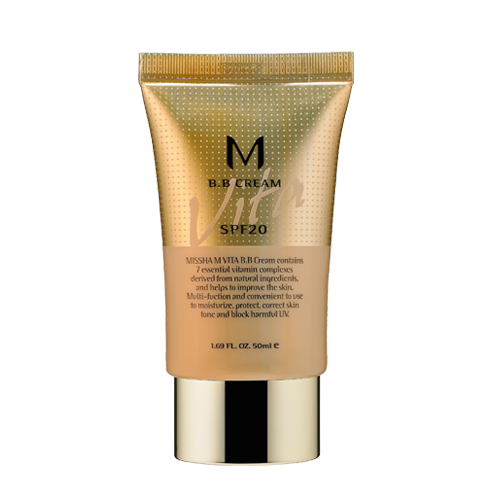 DRUG LABEL: MISSHA M VITA BB
NDC: 13733-006 | Form: CREAM
Manufacturer: ABLE C&C CO., LTD.
Category: otc | Type: HUMAN OTC DRUG LABEL
Date: 20100518

ACTIVE INGREDIENTS: TITANIUM DIOXIDE 3.5 mL/50 mL

Drug Facts

Active Ingredient: TITANIUM DIOXIDE

Inactive Ingredients:
Water, Cyclomethicone, Dimethicone, Butylene Glycol, Bentonite, Silica, Isododecane, 4-Methylbenzylidene Camphor, Hydrogenated Polydecene, Ethylhexyl Methoxycinnamate, Dimethicone/Vinyl Dimethicone Crosspolymer, Sodium Chloride, Polyglyceryl-4 Isostearate, Cetyl PEG/PPG-10/1 Dimethicone, Hexyl Laurate, Glycerin, Beeswax, Sorbitan Sesquioleate, Nylon-12, Disteardimonium Hectorite, Tocopheryl Acetate, Natto Gum, Asparagus Lucidus Root Extract, Tussilago Farfara (Coltsfoot) Flower Extract, Laminaria Japonica Extract, Centella Asiatica Extract, Aloe Barbadensis Leaf Juice, Chamomilla Recutita (Matricaria) Flower Extract, Caviar Extract, Propylene Carbonate, Tourmaline, Amethyst Powder, Coral Powder, Pearl Powder, Limnanthes Alba (Meadowfoam) Seed Oil, Lavandula Angustifolia (Lavender) Flower/Leaf/Stem Extract, Ocimum Basilicum (Basil) Flower/Leaf/Stem Extract, Syringa Vulgaris (Lilac) Extract, Houttuynia Cordata Extract, Angelica Keiskei Leaf/Stem Extract, Rosmarinus Officinalis (Rosemary) Leaf Extract, Althaea Officinals Leaf/Root Extract, Propylene Glycol, Panthenol, Beta-Sitosterol, Cholesterol, Choleth-24, Ceteth-24, Ascorbyl Tetraisopalmitate, Niacinamide, Ubiquinone, DEA-Cetyl Phosphate, Glyceryl Linoleate, Biotin, Glyceryl Linolenate, Glyceryl Arachidonate, Amaranthus Caudatus Seed Extract, Fragrance(Parfum), Propylparaben, Methylparaben, BHT, Disodium EDTA, Limonene, Hydroxyisohexyl 3-Cyclohexane Carboxaldehyde, Linalool, Butylpheryl Methylpropional

DESCRIPTION

Directions: After basic skin care, apply an appropriate amount evenly to the skin according to skin complexion and finish with powder. For enhanced covering effects, use foundation after B.B cream.

Caution: For external use only. Do not swallow. Keep out of reach of children. Avoid contact with eyes.